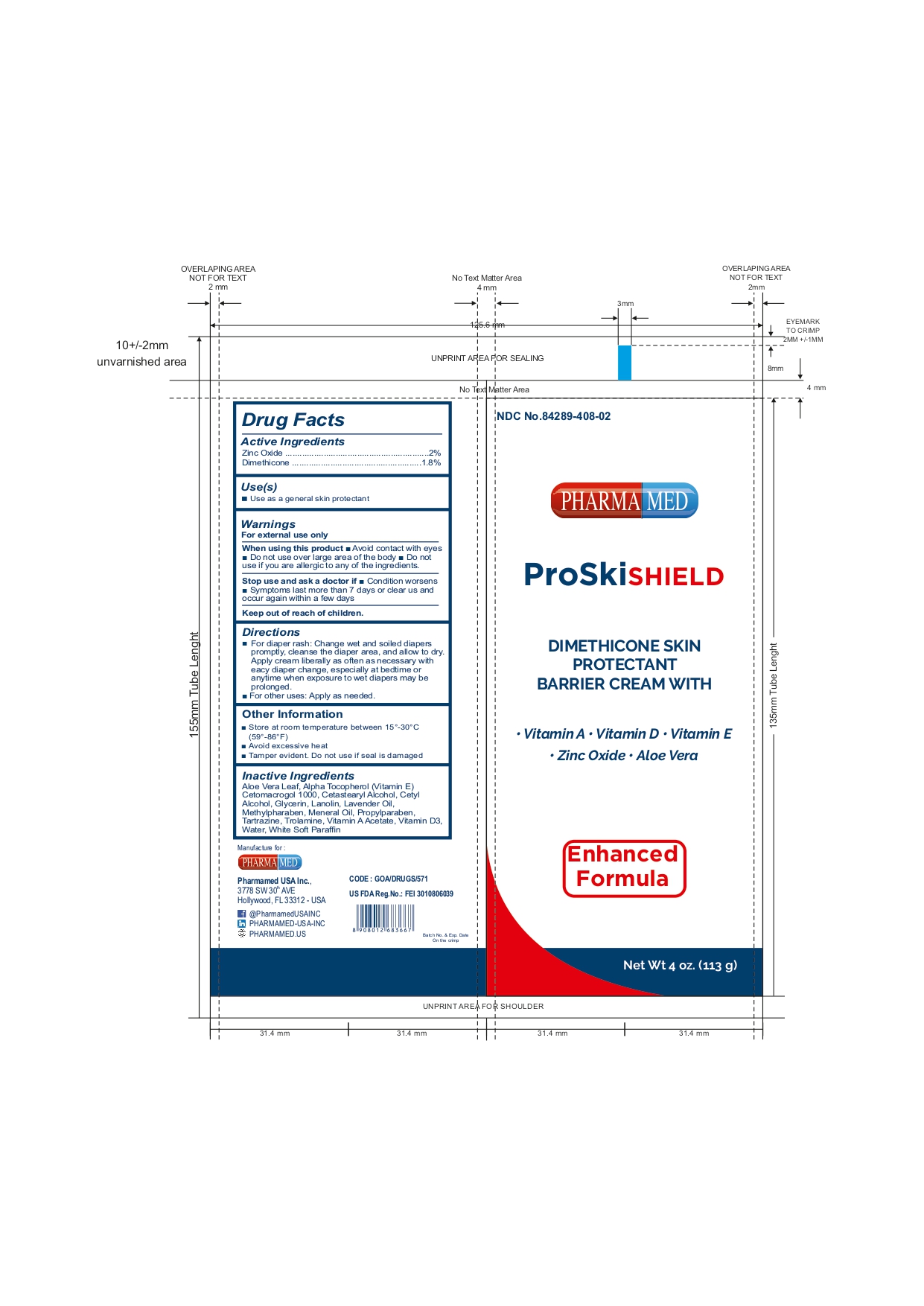 DRUG LABEL: PROSKI SHIELD
NDC: 84289-408 | Form: CREAM
Manufacturer: PHARMAMED USA INC
Category: otc | Type: HUMAN OTC DRUG LABEL
Date: 20250318

ACTIVE INGREDIENTS: ZINC OXIDE 2 g/100 g; DIMETHICONE 1.8 g/100 g
INACTIVE INGREDIENTS: TROLAMINE; WHITE PETROLATUM; CHOLECALCIFEROL; CETOSTEARYL ALCOHOL; GLYCERIN; WATER; PROPYLPARABEN; VITAMIN A ACETATE; ALOE VERA LEAF; ALPHA-TOCOPHEROL; CETETH-20; LAVENDER OIL; YELLOW 5; METHYLPARABEN; CETYL ALCOHOL; LANOLIN; MINERAL OIL

Dimethicone skin protectant with vitamin A,D,E, zinc oxide & aloe Vera.

Active Ingredients

Zinc Oxide 2%

Dimethicone 1.8%

Purpose

- Diaper rash
- Skin Protectant

Uses

- Use as a general skin protectant
- Helps treat chafed skin associated with diaper & nappy rash

Warnings

For External Use Only.

When using this product:

- Avoid contact with eyes
- Do not use over large areas of the body
- So not use if you are alergic to any of the ingredients

Stop use and ask a doctor if:

- Condition worsens
- Symptoms last more than 7 days or clear up and occur again within a few days

Keep out of reach of children:

If swallowed, get medical help or contact a Poison Control Center (1-800-222-1222) right away

Directions

- For diaper rash: Change wet and soiled diapers promptly, cleanse the diaper area, and allow to dry. Apply cream liberally as often as necessary with each diaper change, especially at bedtime or anytime when exposure to wet diapers may be prolonged.
- For other uses: Apply as needed.

Other Information

- Store at room temperature between 15º - 30ºC (59º - 86ºF)
- Avoid excessive heat
- Tamper evident. Do not use if the seal is damaged.

Inactive Ingredients

Aloe Vera Leaf, Alpha-Tocopherol (Vitamin E), CETETH-20, Cetostearyl Alcohol, Cetyl Alcohol, Glycerin, Lanolin, Lavender Oil, Methylparaben, Mineral Oil, Propylparaben, Yellow 5, Trolamine, Vitamin A Acetate, Vitamin D3, Water, White Petrolatum

Questions and Comments?

(754)-200-8994 (Mon-Fri 8 AM to 4 PM EST)

Package/Label Principal Display Panel

NDC: 84289-408-02

DIMETHICONE SKIN PROTECTANT BARRIER CREAM WITH

■ Vitamin A ■ Vitamin D ■ Vitamin E ■ Zinc Oxide ■ Aloe Vera

Enhanced Formula

Net Wt 4 oz. (113 g)

GOA/DRUGS/571